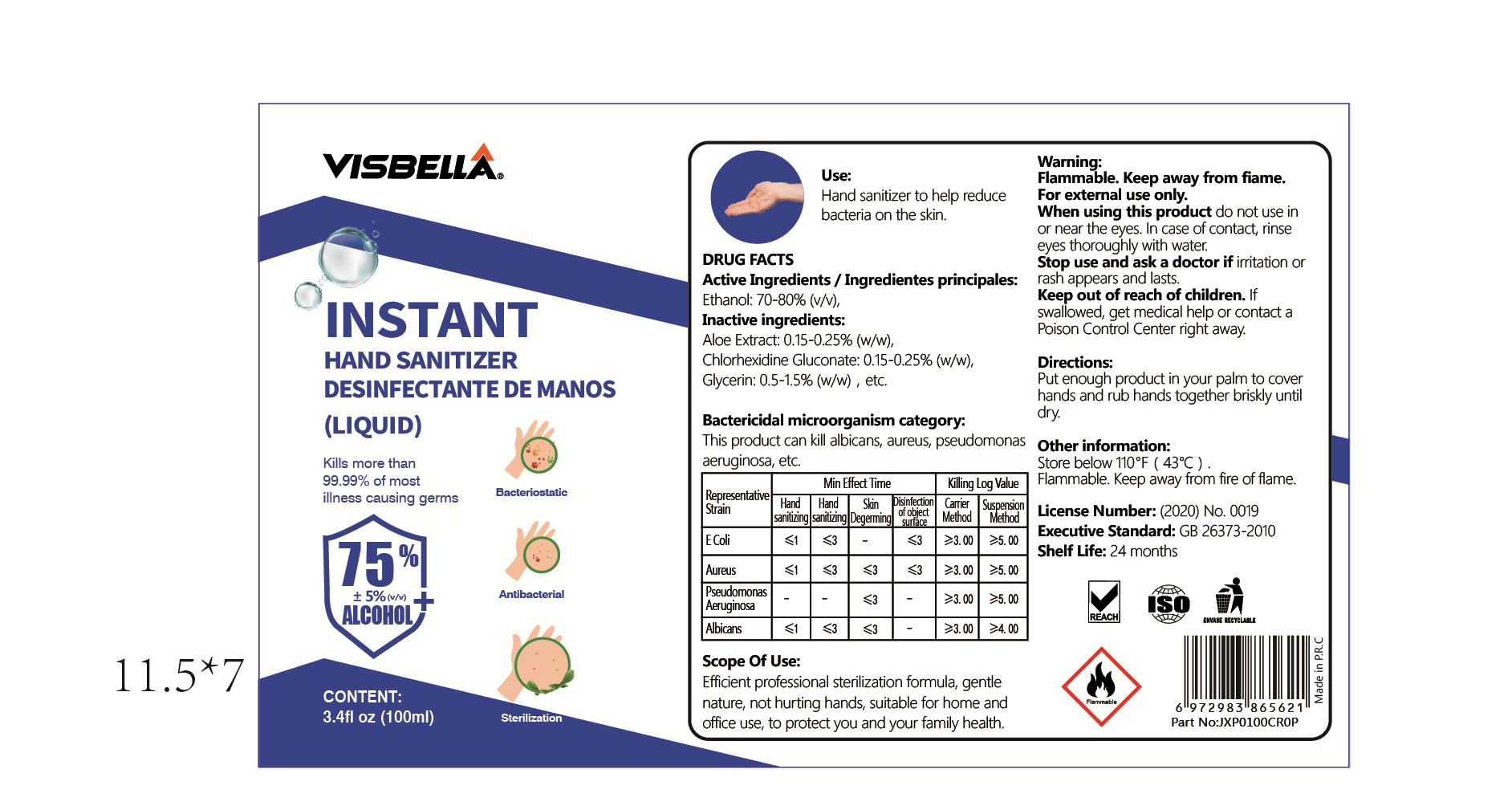 DRUG LABEL: VISBELLA instant hand sanitizer desinfectante de manos
NDC: 40760-004 | Form: LIQUID
Manufacturer: Huzhou Guoneng New Material Co., Ltd.
Category: otc | Type: HUMAN OTC DRUG LABEL
Date: 20200708

ACTIVE INGREDIENTS: ALCOHOL 75 mL/100 mL
INACTIVE INGREDIENTS: ALOE; GLYCERIN; CHLORHEXIDINE GLUCONATE

INACTIVE INGREDIENT

aloe extract,chlorhexidine gluconate， glycerin

INDICATIONS AND USAGE

Efficient professional sterilization formula, gentle nature, not hurting hands, suitable for home and office use, to protect you and your family health.

ACTIVE INGREDIENT

alcohol

keep out of reach of children

PURPOSE

Disinfection
Sterilization
No Rinseing

WARNINGS

For extermal use only.
When using this product do not use in or near the eyes. In case of contact, rinse eyes thoroughly with water.
Stop use and ask a doctor if rritation or rash appears and lasts.
Keep out of reach of children.

DOSAGE AND ADMINISTRATION

Store below 110°F (43°C) .
Flammable. Keep away from fire of flame.